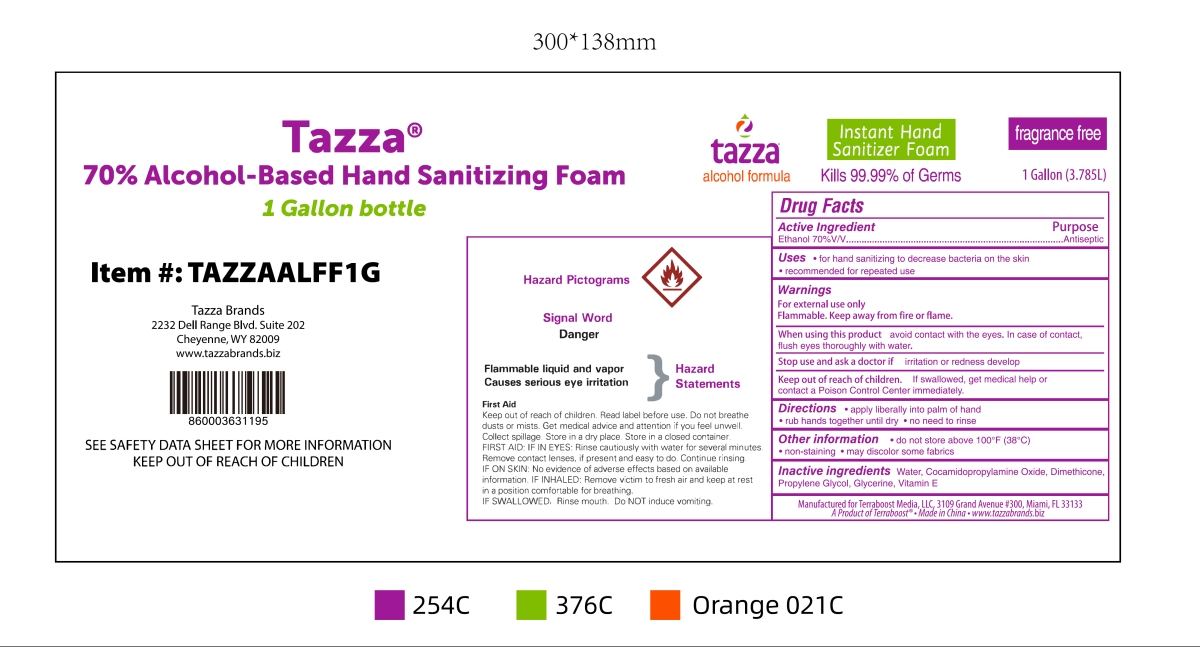 DRUG LABEL: Tazza 70% Alcohol-Based Hand Sanitizing Foam
NDC: 76370-0033 | Form: LIQUID
Manufacturer: Tazza Brands East, Inc.
Category: otc | Type: HUMAN OTC DRUG LABEL
Date: 20251224

ACTIVE INGREDIENTS: ALCOHOL 70 L/100 L
INACTIVE INGREDIENTS: COCAMIDOPROPYLAMINE OXIDE; WATER; GLYCERIN; DIMETHICONE; PROPYLENE GLYCOL; .ALPHA.-TOCOPHEROL

76370-0033 Tazza 70% Alcohol-Based Hand Sanitizing Foam

Active Ingredient

Ethanol 70%V/V

Purpose

Antiseptic

INDICATIONS AND USAGE

Uses ·for hand sanitizing to decrease bacteria on the skin

·recommended for repeated use

Warnings

For external use only

Flammable.Keep away from fire or flame.

When using this product avoid contact with the eyes.In case of contact,

flush eyes thoroughly with water.

Stop use and ask a doctor if irritation or redness develop

Keep out of reach of children. If swallowed, get medical help or

contact a Poison Control Center immediately.

DOSAGE AND ADMINISTRATION

Directions ·apply liberally into palm of hand

·rub hands together until dry ·no need to rinse

Other information ·do not store above 100°F(38℃)

·non-staining ·may discolor some fabrics

Inactive ingredients Water, Cocamidopropylamine Oxide, Dimethicone,

Propylene Glycol, Glycerine, Vitamin E

PACKAGE LABEL

Tazza
70% Alcohol-Based Hand Sanitizing Foam
1 Gallon bottle
NDC: 76370-0033-0